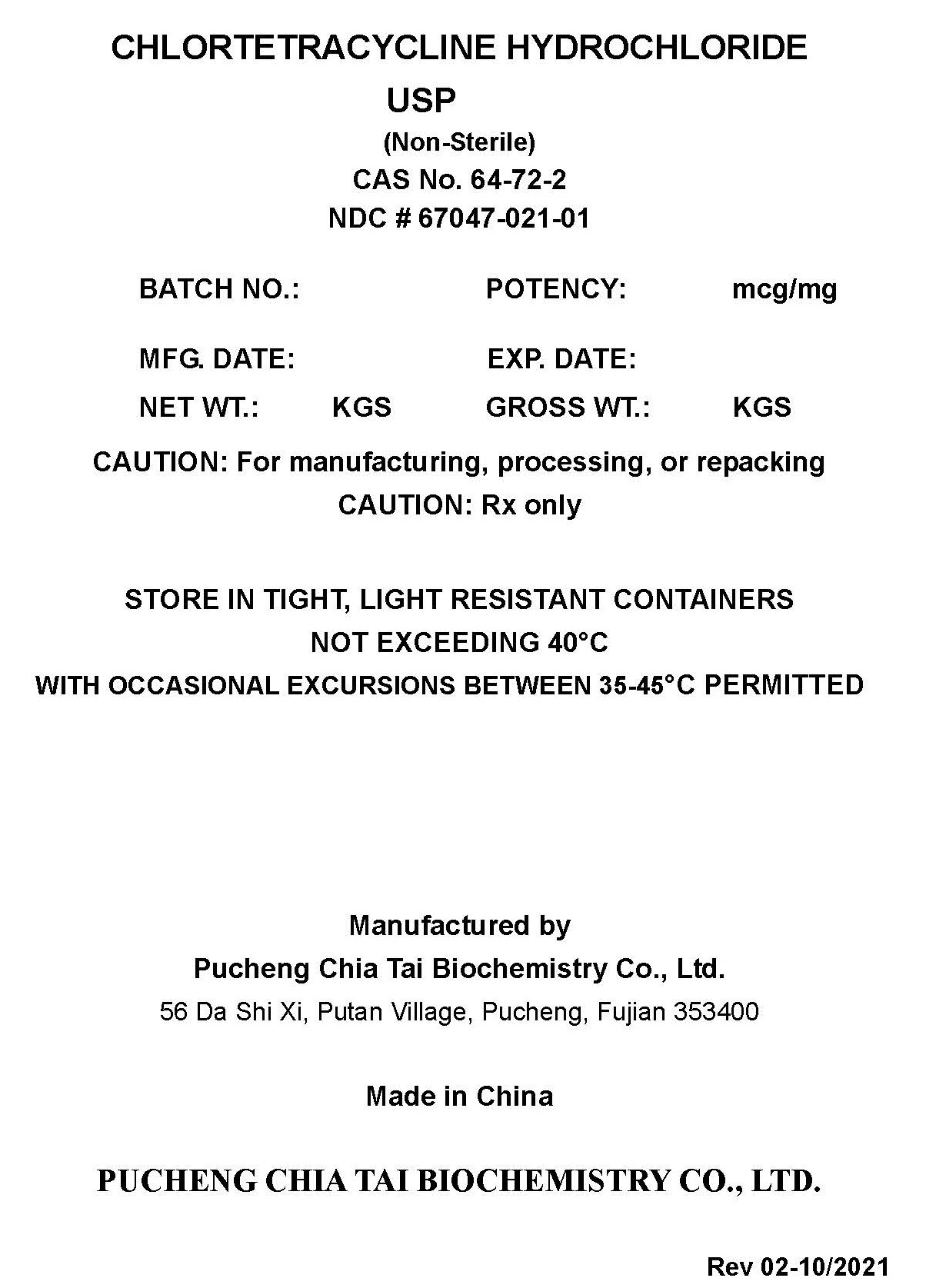 DRUG LABEL: Chlortetracycline Hydrochloride
NDC: 67047-021 | Form: POWDER
Manufacturer: Pucheng Chia Tai Biochemistry Co. Ltd.
Category: other | Type: BULK INGREDIENT - ANIMAL DRUG
Date: 20211022

ACTIVE INGREDIENTS: Chlortetracycline Hydrochloride 1 kg/1 kg

CHLORTETRACYCLINE HYDROCHLORIDE

PACKAGE LABEL

CHLORTETRACYCLINE HYDROCHLORIDE

USP

(Non-Sterile)
CAS No. 64-72-2
NDC # 67047- 021- 01

BATCH NO.:
POTENCY:
mcg/mg

MFG. DATE:
EXP. DATE:

NET WT.:
kg
GROSS WT.:
kg

CAUTION: For manufacturing, processing or repacking

CAUTION: Rx only

STORE IN TIGHT, LIGHT RESISTANT CONTAINERS
NOT EXCEEDING 40°C
WITH OCCASIONAL EXCURSIONS BETWEEN 35-45 °C PERMITTED

Manufactured by

Pucheng Chia Tai Biochemistry Co., Ltd.
56 Da Shi Xi, Putan Village, Pucheng, Fujian 353400

Made in China

PUCHENG CHIA TAI BIOCHEMISTRY CO., LTD.

Rev 02-10/2021